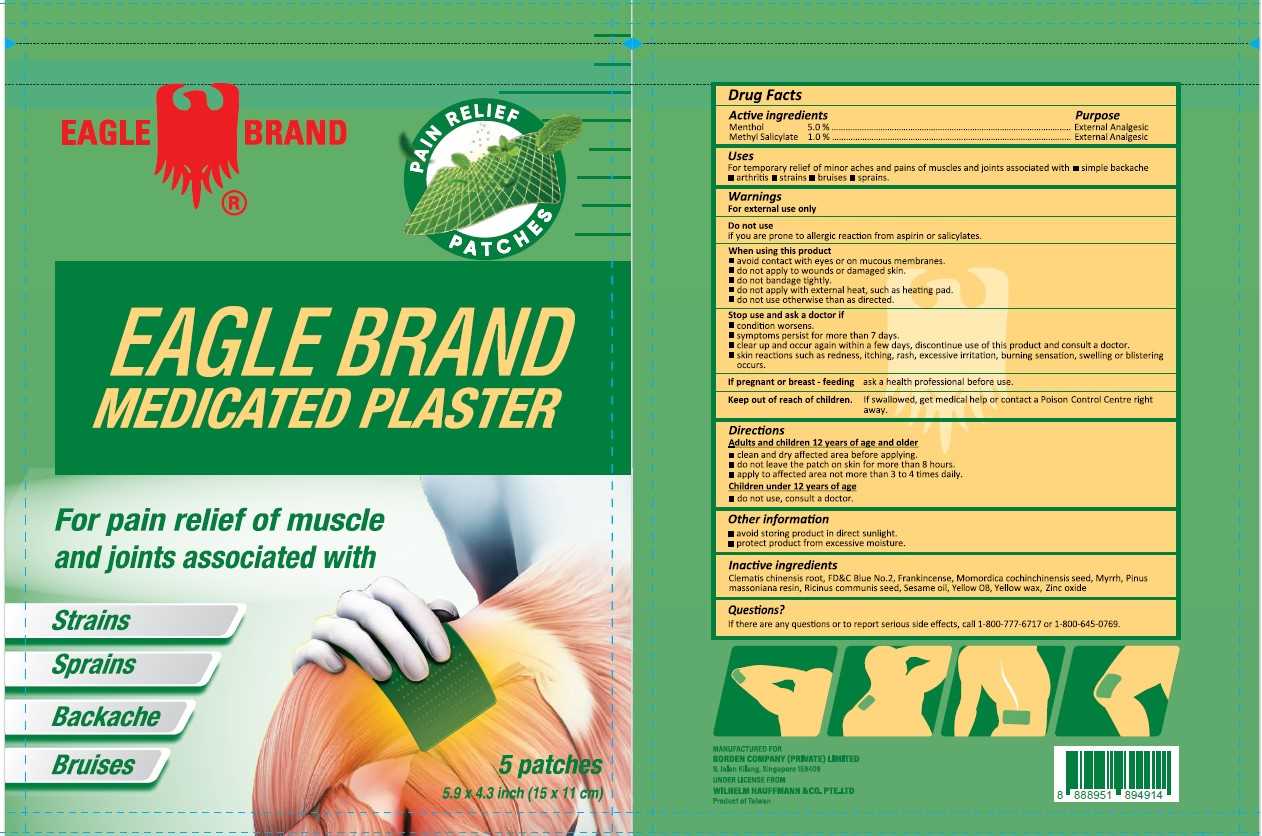 DRUG LABEL: Eagle Brand
NDC: 43405-300 | Form: PATCH
Manufacturer: Borden Company (Private) Limited
Category: otc | Type: HUMAN OTC DRUG LABEL
Date: 20240130

ACTIVE INGREDIENTS: MENTHOL 5 g/100 g; METHYL SALICYLATE 1 g/100 g
INACTIVE INGREDIENTS: SESAME OIL; FRANKINCENSE; MYRRH; ZINC OXIDE; YELLOW OB; FD&C BLUE NO. 2; PINUS MASSONIANA RESIN; CLEMATIS CHINENSIS ROOT; YELLOW WAX; MOMORDICA COCHINCHINENSIS SEED; RICINUS COMMUNIS SEED

Eagle Brand Medicated Plaster

Active ingredients

Menthol 5.0%

Methyl Salicylate 1.0%

Purpose

External Analgesic

Uses

For temporary relief of minor aches and pains of muscles and joints associated with ▪ simple backache ▪ arthritis ▪ strains ▪ bruises ▪ sprains.

Warnings

For external use only.

When using this product

▪ Avoid contact with eyes or on mucous membranes.

▪ Do not apply to wounds or damaged skin.

▪ Do not bandage tightly.

▪ Do not apply wiht external heat, such as heating pad.

▪ Do not use otherwise than as directed.

Stop use and ask a doctor if

▪ Condition worsens.

▪ Symptoms persist for more than 7 days.

▪ Clear up and occur again within a few days, discontinue use of this product and consult a doctor.

▪ Skin reactions such as redness, itching, rash, excessive irritation, burning sensation, swelling or blistering occurs.

If pregnant or breast-feeding

Ask a health professional before use.

Keep out of reach of children

If swallowed, get medical help or contact a Poison Control Centre right away.

Directions

Adults and children 12 years of age and above:

▪ Clean and dry affected area before applying.

▪ Do not leave the patch on skin for more than 8 hours.

▪ Apply to affected area not more than 3 to 4 times daily.

Children under 12 years of age:

▪ Do not use, consult a doctor.

Other information

▪ Avoid storing product in direct sunlight.

▪ Protect product from excessive moisture.

Inactive ingredients

Clematis chinensis root, FD&C Blue No.2, Frankincense, Momordica cochinchinensis seed, Myrrh, Pinus massoniana resin, Ricinus communis seed, Sesame oil, Yellow OB, Yellow wax, Zinc oxide

Questions?

If there are any questions or to report serious side effects, call 1-800-777-6717 or 1-800-645-0769.

Package Label

5 Patches Pouch NDC: 43405-300-05